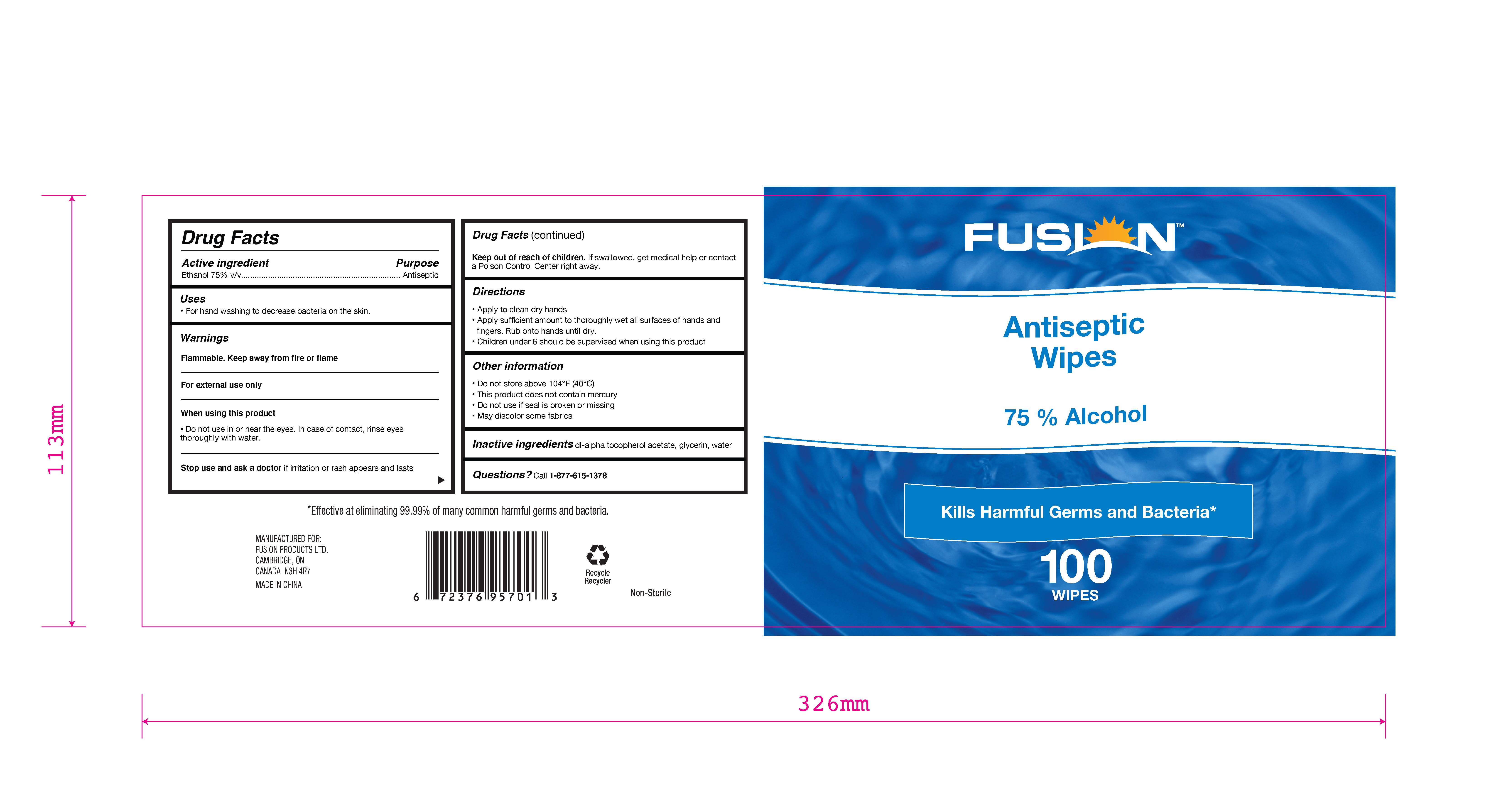 DRUG LABEL: Fusion Antiseptic Wipes
NDC: 80336-005 | Form: CLOTH
Manufacturer: Fusion Products Ltd.
Category: otc | Type: HUMAN OTC DRUG LABEL
Date: 20210617

ACTIVE INGREDIENTS: ALCOHOL 0.75 1/1 1
INACTIVE INGREDIENTS: WATER; GLYCERIN; .ALPHA.-TOCOPHEROL ACETATE

Fusion Antiseptic Wipes

Active Ingredient

Ethanol 75% v/v

Uses

For hand washing to decrease bacteria on the skin.

Warnings

Flammable. Keep away from fire or flame.

For external use only

When using this product

Do not use in or near the eyes. In case of contact, rinse eyes thoroughly with water.

Stop use and ask a doctor if irritation or rash appears and lasts.

Keep out of reach of children. If swallowed,get medical help or contact a Poison Control Center right away.

When using this product

Do not use in or near the eyes. In case of contact, rinse eyes thoroughly with water.

Stop use and ask a doctor if irritation or rash appears and lasts.

Keep out of reach of children. If swallowed,get medical help or contact a Poison Control Center right away.

Directions

Apply to clean dry hands.

Apply sufficient amount to thoroughly wet all surfaces of hands and fingers. Rub onto hands until dry.

Children under 6 should be supervised when using this product.

Other information

Do not store above 104°F (40°C).

This product does not contain mercury.

Do not use if seal is broken or missing.

May discolor some fabrics.

Inactive ingredients

dl-alpha tocopherol acetate, glycerin, water

Purpose

Antiseptic

PACKAGE LABEL

100 WIPES, NDC: 80336-005-05